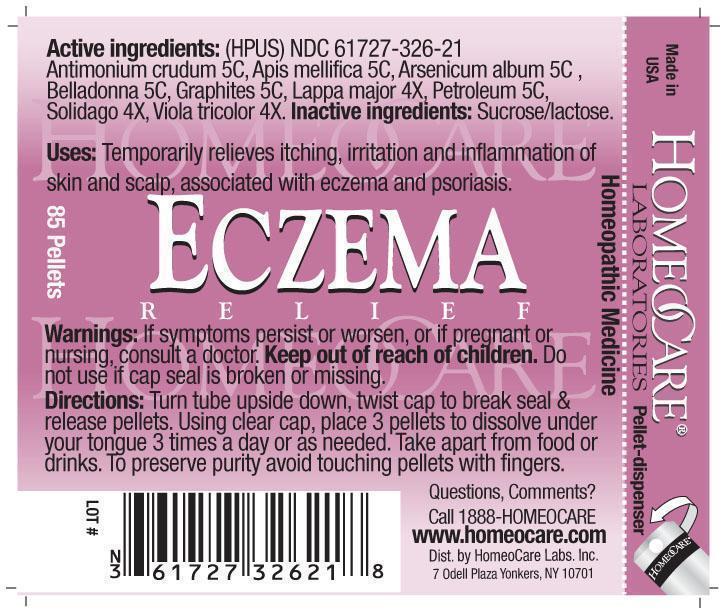 DRUG LABEL: Eczema Relief
NDC: 61727-326 | Form: PELLET
Manufacturer: Homeocare Laboratories
Category: homeopathic | Type: HUMAN OTC DRUG LABEL
Date: 20181231

ACTIVE INGREDIENTS: ANTIMONY TRISULFIDE 5 [hp_C]/4 g; APIS MELLIFERA 5 [hp_C]/4 g; ARSENIC TRIOXIDE 5 [hp_C]/4 g; ATROPA BELLADONNA 5 [hp_C]/4 g; GRAPHITE 5 [hp_C]/4 g; ARCTIUM LAPPA FRUIT 4 [hp_X]/4 g; KEROSENE 5 [hp_C]/4 g; SOLIDAGO CANADENSIS WHOLE 4 [hp_X]/4 g; VIOLA TRICOLOR 4 [hp_X]/4 g
INACTIVE INGREDIENTS: SUCROSE; LACTOSE

Eczema Relief

Active Ingredients:

Antimonium crudum 5C, Apis mellifica 5C, Arsenicum album 5C, Belladonna 5C, Graphites 5C, Lappa major 4X, Petroleum 5C, Solidago 4X, Viola tricolor 4X.

Inactive Ingredients:

Sucrose/lactose.

Purpose:

Temporarily relieves itching, irritation and inflammation of skin and scalp, associated with eczema and psoriasis.

Keep out of reach of children.

Indications & Usage:

Turn tube upside down, twist cap to break seal & release pellets. Using clear cap, place 3 pellets to dissolve under your tongue 3 times a day or as needed. Take apart from food or drinks. To preserve purity avoid touching pellets with fingers.

Warnings:

If symptoms persist or worsen, or if pregnant or nursing, consult a doctor. Keep out of reach of children. Do not use if cap seal is broken or missing.

Dosage & Administration:

Turn tube upside down, twist cap to break seal & release pellets. Using clear cap, place 3 pellets to dissolve under your tongue 3 times a day or as needed. Take apart from food or drinks. To preserve purity avoid touching pellets with fingers.

Eczema Relief

Homeopathic Medicine

85 Pellets

hcl_label_eczema 2012.jpg